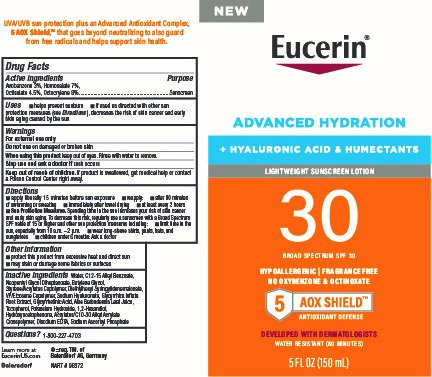 DRUG LABEL: Eucerin Advance Hydration Sunscreen SPF 30
NDC: 66800-3000 | Form: LOTION
Manufacturer: Beiersdorf Inc
Category: otc | Type: HUMAN OTC DRUG LABEL
Date: 20251231

ACTIVE INGREDIENTS: OCTOCRYLENE 8 g/100 g; AVOBENZONE 3 g/100 g; HOMOSALATE 7 g/100 g; OCTISALATE 4.5 g/100 g
INACTIVE INGREDIENTS: WATER; NEOPENTYL GLYCOL DIHEPTANOATE; STYRENE/ACRYLAMIDE COPOLYMER (MW 500000); DIETHYLHEXYL SYRINGYLIDENEMALONATE; VINYLPYRROLIDONE/EICOSENE COPOLYMER; GLYCYRRHIZA INFLATA ROOT; ENOXOLONE; ALOE VERA LEAF; TOCOPHEROL; CARBOMER INTERPOLYMER TYPE A (ALLYL SUCROSE CROSSLINKED); EDETATE DISODIUM; ALKYL (C12-15) BENZOATE; BUTYLENE GLYCOL; HYALURONATE SODIUM; POTASSIUM HYDROXIDE; 1,2-HEXANEDIOL; HYDROXYACETOPHENONE; SODIUM ASCORBYL PHOSPHATE

Eucerin Advanced Hyration Lotion Sunscreen SPF 30

Active ingredients

Avobenzone 3%, Homosalate 7%, Octisalate 4.5%, Octocrylene 8%

Purpose

Sunscreen

Uses

■ helps prevent sunburn

■ if used as directed with other sun protection measures (see Directions), decreases the risk of skin cancer and early skin aging caused by the sun

Warnings

For external use only

Do not useon damaged or broken skin

WHEN USING

When using this productkeep out of eyes. Rinse with water to remove.

Stop use and ask a doctor ifrash occurs

Keep out of reach of children.If product is swallowed, get medical help or contact a Poison Control Center right away.

Directions

■ apply liberally 15 minutes before sun exposure

■ reapply:

■ after 80 minutes of swimming or sweating

■ immediately after towel drying

■ at least every 2 hours

■ Sun Protection Measures. Spending time in the sun increases your risk of skin cancer and early skin aging. To decrease this risk, regularly use a sunscreen with a Broad Spectrum SPF value of 15 or higher and other sun protection measures including:

■ limit time in the sun, especially from 10 a.m. – 2 p.m.

■ wear long-sleeve shirts, pants, hats, and sunglasses

■ children under 6 months: Ask a doctor

Other information

■ protect this product from excessive heat and direct sun

■ may stain or damage some fabrics or surfaces

Inactive ingredients

Water, C12-15 Alkyl Benzoate, Neopentyl Glycol Diheptanoate, Butylene Glycol, Styrene/Acrylates Copolymer, Diethylhexyl Syringylidenemalonate, VP/Eicosene Copolymer, Sodium Hyaluronate, Glycyrrhiza Inflata Root Extract, Glycyrrhetinic Acid, Aloe Barbadensis Leaf Juice, Tocopherol, Potassium Hydroxide, 1,2-Hexandiol, Hydroxyacetophenone, Acrylates/C10-30 Alkyl Acrylate Crosspolymer, Disodium EDTA, Sodium Ascorbyl Phosphate

Questions?

1-800-227-4703

PACKAGE LABEL

Eucerin®

Advanced Hydration

+Hyaluronic Acid & Humectants

Lightweight Sunscreen Lotion

30 Broad Spectrum SPF 30

Hypoallergenic | Fragrance Free

No Oxybenzone & Octinoxate

5 AOX Shield™

Antioxidant Defense

Developed with Dermatologists

Water Resistant (80 Minutes)

5 FL OZ (150 mL)